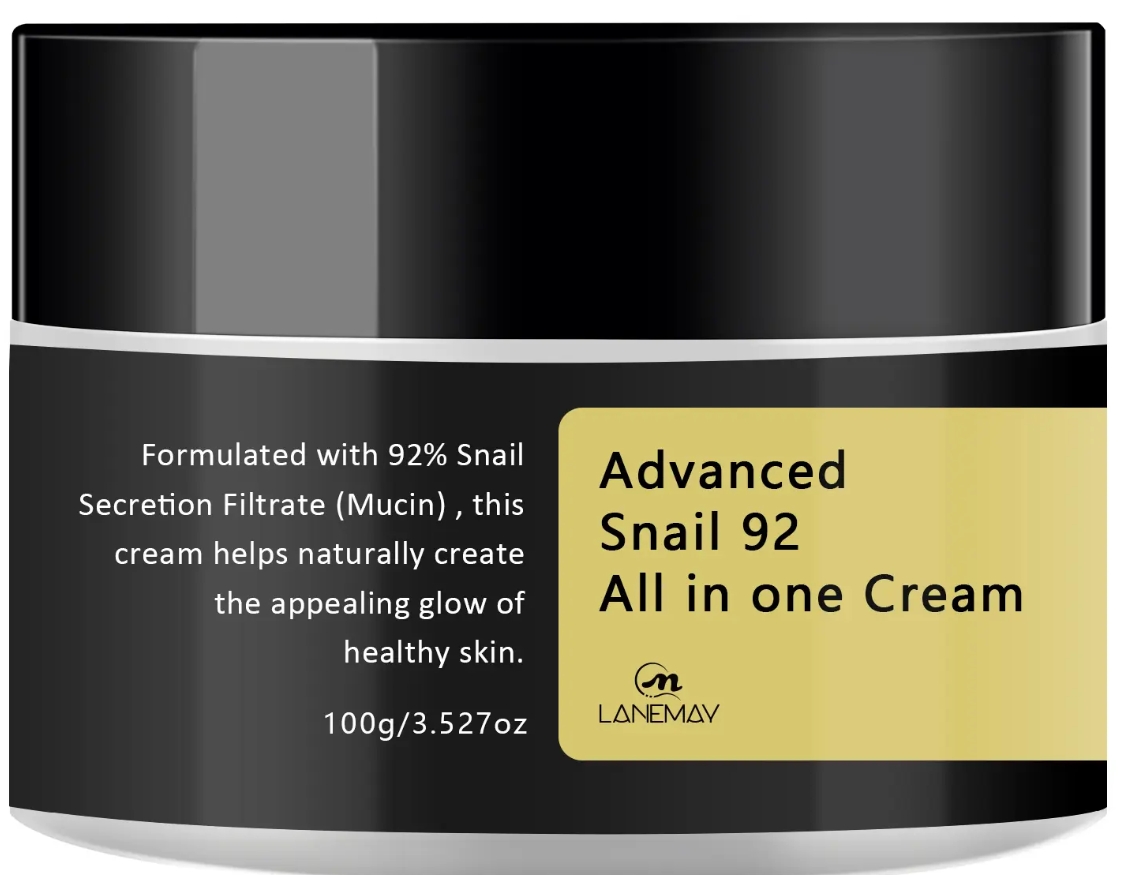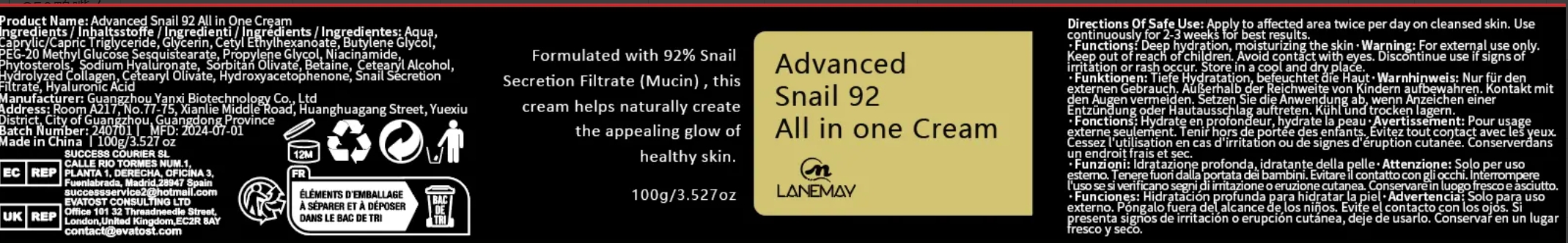 DRUG LABEL: Advanced Snail 92 All inOne Cream
NDC: 84025-192 | Form: CREAM
Manufacturer: Guangzhou Yanxi Biotechnology Co.. Ltd
Category: otc | Type: HUMAN OTC DRUG LABEL
Date: 20240923

ACTIVE INGREDIENTS: CETYL ETHYLHEXANOATE 3 mg/100 g; GLYCERIN 5 mg/100 g
INACTIVE INGREDIENTS: WATER

DOSAGE AND ADMINISTRATION

Cream for whitening skin and enhancing facial skin radiance

INDICATIONS AND USAGE

For daily skin care

INACTIVE INGREDIENT

AQUA

WARNINGS

Keep out of children

Keep out of children

PURPOSE

Moisturizes the skin and effectively enhances skin radiance.